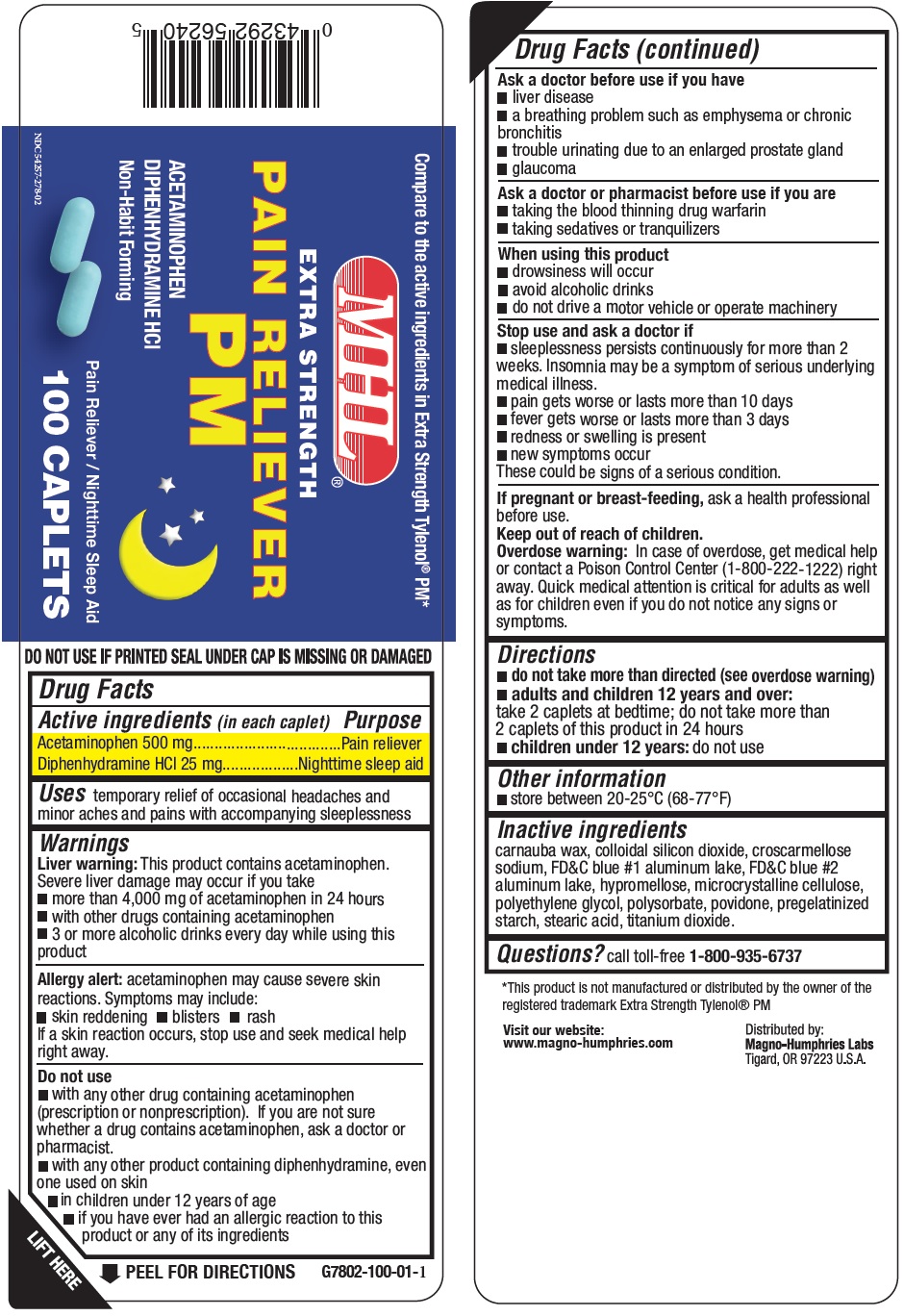 DRUG LABEL: Pain Reliever PM
NDC: 54257-278 | Form: TABLET
Manufacturer: Magno-Humphries, Inc.
Category: otc | Type: HUMAN OTC DRUG LABEL
Date: 20231027

ACTIVE INGREDIENTS: ACETAMINOPHEN 500 mg/1 1; DIPHENHYDRAMINE HYDROCHLORIDE 25 mg/1 1
INACTIVE INGREDIENTS: CARNAUBA WAX; SILICON DIOXIDE; CROSCARMELLOSE SODIUM; FD&C BLUE NO. 1; ALUMINUM OXIDE; FD&C BLUE NO. 2; HYPROMELLOSE, UNSPECIFIED; MICROCRYSTALLINE CELLULOSE; POLYETHYLENE GLYCOL, UNSPECIFIED; POVIDONE; STEARIC ACID; TITANIUM DIOXIDE

Pain Reliever PM

Active ingredient (in each caplet)

Acetaminophen 500 mg

Diphenhydramine HCl 25 mg

Purpose

Nighttime sleep aid

Uses

temporary relief of occasional headaches and minor aches and pains with accompanying sleeplessness

Warnings

This product contains acetaminophen. Severe liver damage may occur if you take Liver warning:

acetaminophen may cause severe skin reactions. Symptoms may include: Allergy alert:

If a skin reaction occurs, stop use and seek medical help right away.

- more than 4,000 mg of acetaminophen in 24 hours
- with other drugs containing acetaminophen
- 3 or more alcoholic drinks every day while using this product

- skin reddening
- blisters
- rash

Do not use

- with any other drug containing acetaminophen (prescription or nonprescription). If you are not sure whether a drug contains acetaminophen, ask a doctor or pharmacist.
- with any other product containing diphenhydramine, even one used on skin
- in children under 12 years of age
- if you have ever had an allergic reaction to this product or any of its ingredients

Ask a doctor before use if you have

- liver disease
- a breathing problem such as emphysema or chronic bronchitis
- trouble urinating due to an enlarged prostate gland
- glaucoma

Ask a doctor or pharmacist before use if you are

- taking the blood thinning drug warfarin
- taking sedatives or tranquilizers

When using this product

- drowsiness will occur
- avoid alcoholic drinks
- do not drive a motor vehicle or operate machinery

Stop use and ask a doctor if

- sleeplessness persists continuously for more than 2 weeks. Insomnia may be a symptom of serious underlying medical illness.
- pain gets worse or lasts more than 10 days
- fever gets worse or lasts more than 3 days
- redness or swelling is present
- new symptoms occur These could be signs of a serious condition.

If pregnant or breast-feeding,

ask a health professional before use.

Keep out of reach of children.

In case of overdose, get medical help or contact a Poison Control Center (1-800-222-1222) right away. Quick medical attention is critical for adults as well as for children even if you do not notice any signs or symptoms. Overdose warning:

Directions

- do not take more than directed (see overdose warning)
- take 2 caplets at bedtime; do not take more than 2 caplets of this product in 24 hours adults and children 12 years and over:
- do not use children under 12 years:

Other information

- store between 20º to 25ºC (68º to 77º F)

Inactive ingredients

carnauba wax, colloidal silicon dioxide, croscarmellose sodium, FD&C blue #1 aluminum lake, FD&C blue #2 aluminum lake, hypromellose, microcrystalline cellulose, polyethylene glycol, polysorbate, povidone, pregelatinized starch, stearic acid, titanium dioxide.

Questions?

call toll-free 1-800-935-6737